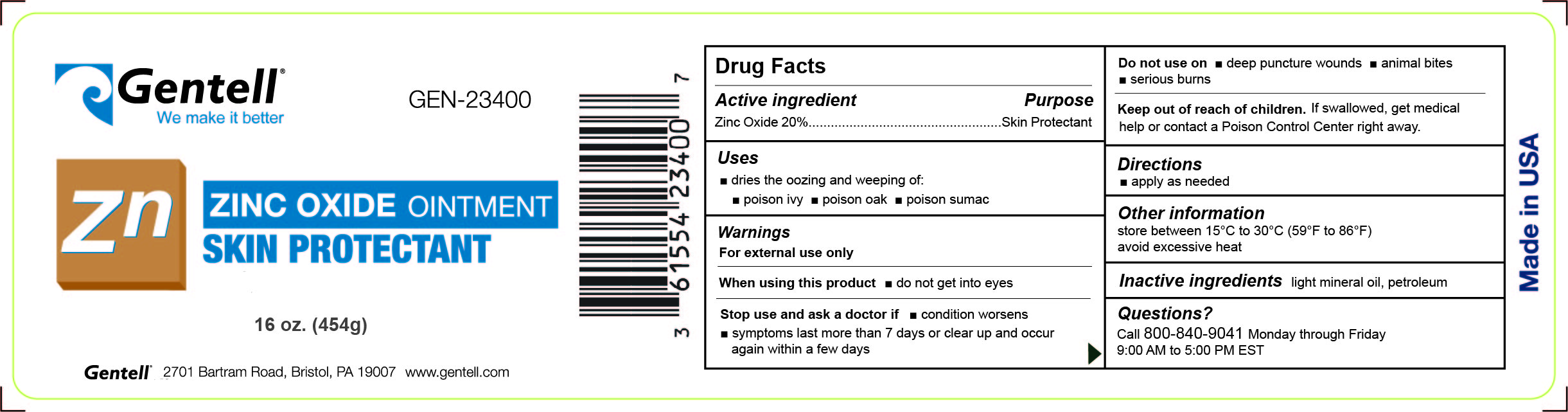 DRUG LABEL: Zinc Oxide
NDC: 61554-100 | Form: OINTMENT
Manufacturer: Gentell, Inc.
Category: otc | Type: HUMAN OTC DRUG LABEL
Date: 20240808

ACTIVE INGREDIENTS: ZINC OXIDE 0.2 g/1 g
INACTIVE INGREDIENTS: PETROLATUM 0.75 g/1 g; LIGHT MINERAL OIL 0.05 g/1 g

Zinc Oxide Ointment

ACTIVE INGREDIENT

Zinc Oxide 20%

PURPOSE

Skin Protectant

Uses

dries the oozing and weeping of:

- poison ivy
- poison oak
- poison sumac

Warnings

For external use only

When using this product

- do not get into eyes

Stop use and ask a doctor if

- condition worsens
- symptoms last more than 7 days or clear up and occur again within a few days

Do not use on

- deep puncture wounds
- animal bites
- serious burns

Keep out of reach of children. If swallowed, get medical help or contact a Poison Control Center right away.

When using this product

- do not get into eyes

Stop use and ask a doctor if

- condition worsens
- symptoms last more than 7 days or clear up and occur again within a few days

Stop use and ask a doctor if

- condition worsens
- symptoms last more than 7 days or clear up and occur again within a few days

Do not use on

- deep puncture wounds
- animal bites
- serious burns

Keep out of reach of children.

OTHER SAFETY INFORMATION

For external use only

If swallowed, get medical help or contact a Poison Control Center right away.

Directions

- apply as needed

DOSAGE AND ADMINISTRATION

apply as needed

Other Information

store between 15ºC to 30ºC (59ºF to 86ºF)

avoid excessive heat

Inactive ingredients

light mineral oil, petrolatum

Questions?

Call 800-840-9041 Monday through Friday 9:00 AM to 5:00 PM EST

PACKAGE LABEL

Gentell® We make it better

GEN-23400

Zn Oxide

Zinc Oxide Ointment

Skin Protectant

16 oz. (454g)

Gentell 2701 Bartram Road, Bristol, PA 19007 www.gentell.com